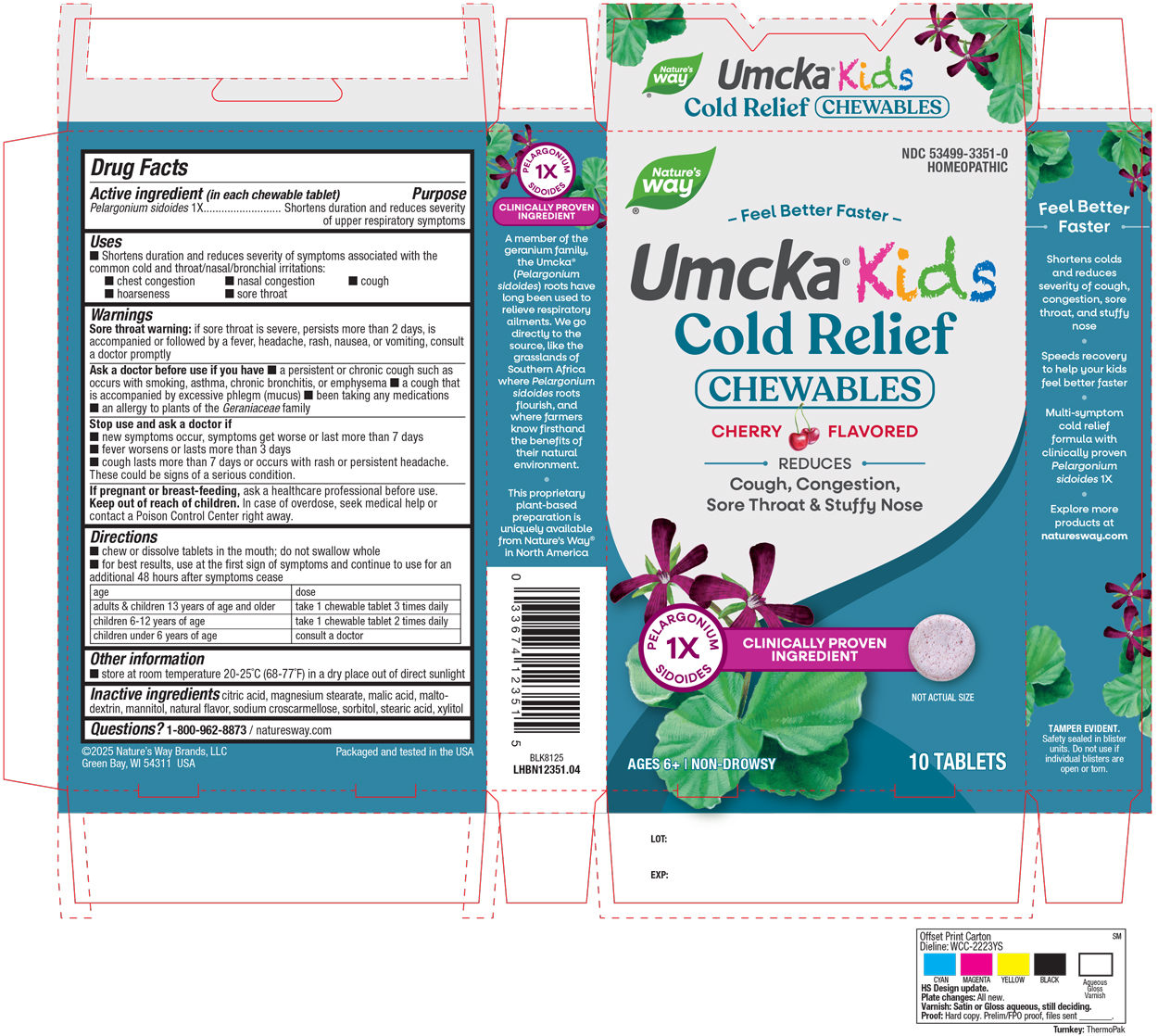 DRUG LABEL: Cold Relief Kids Cherry
NDC: 53499-3351 | Form: TABLET, CHEWABLE
Manufacturer: Schwabe North America, Inc
Category: homeopathic | Type: HUMAN OTC DRUG LABEL
Date: 20250828

ACTIVE INGREDIENTS: PELARGONIUM SIDOIDES ROOT 1 [hp_X]/1 1
INACTIVE INGREDIENTS: ANHYDROUS CITRIC ACID; MAGNESIUM STEARATE; MALIC ACID; MALTODEXTRIN; MANNITOL; CROSCARMELLOSE SODIUM; SORBITOL; STEARIC ACID; XYLITOL

Cold Relief Kids Cherry 10 chew tabs

Active Ingredient

Pelargonium sidoides 1X

Inactive Ingredients

Citric Acid

Magnesium Stearate

Malic Acid

Maltodextrin

Mannitol

Natural Flavor

Sodium Croscarmellose

Sorbitol

Stearic Acid

Xylitol

Dosage and Administration

Directions

Chew or dissolve tablets in the mouth. Do not swallow whole.

For best results, use at the first sign of symptoms and continue to use for an additional 48 hours after symptoms cease.
Adults & children 13 years of age and older: Take 1 chewable tablet three times daily.
Children 6-12 years of age: Take 1 chewable tablet two times daily.
Children under 6 years of age: Consult a doctor.

Indications & Usage

Shortens duration and reduces severity of symptoms associated with the common cold and throat/nasal/bronchial irritations: chest congestion, nasal congestion, cough, hoarseness, sore throat.

Purpose

Shortens duration and reduces severity of symptoms associated with the common cold and throat/nasal/bronchial irritations: chest congestion, nasal congestion, cough, hoarseness, sore throat.

Warnings

Sore throat warning: if sore throat is severe, persists more than 2 days, is accompanied or followed by a fever, headache, rash, nausea, or vomiting, consult a doctor promptly.

Ask a doctor before use if you have a persistent or chronic cough such as occurs with smoking, asthma, chronic bronchitis, or emphysema, a cough that is accompanied by excessive phlegm (mucus), been taking any medications, an allergy to plants of the Geraniaceae family.

Stop Use

Stop use and ask a doctor if new symptoms occur, symptoms get worse or last more than 7 days, fever worsens or lasts more than 3 days, cough lasts more than 7 days or occurs with rash or persistent headache.

These could be signs of a serious condition.

Pregnancy or Breast Feeding

If you are pregnant or breast-feeding, ask a healthcare professional before use.

Keep out of reach of children

Keep out reach of children.

Overdose

In case of overdose, seek medical help or contact a Posion Control Center right away.